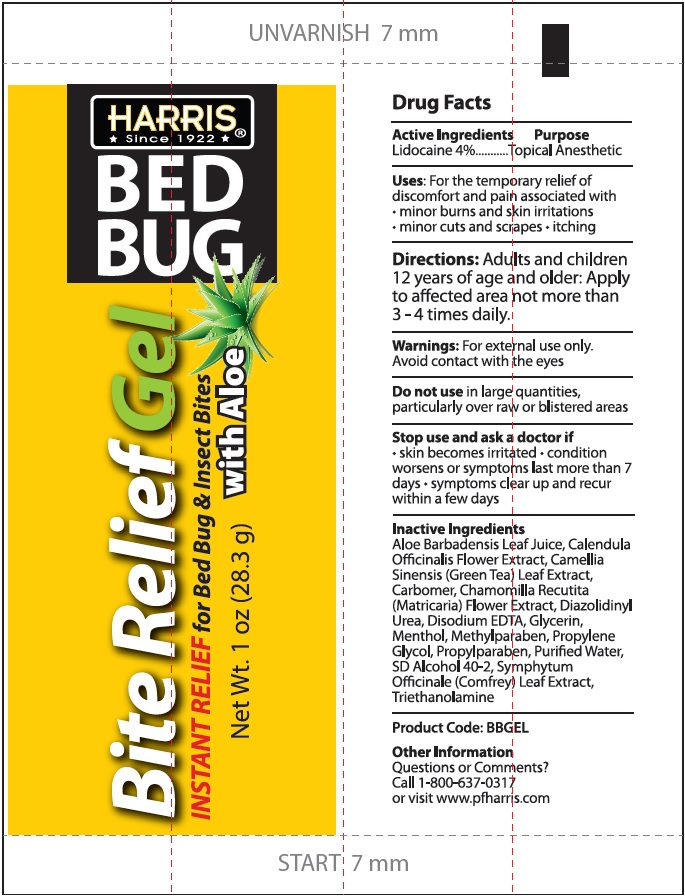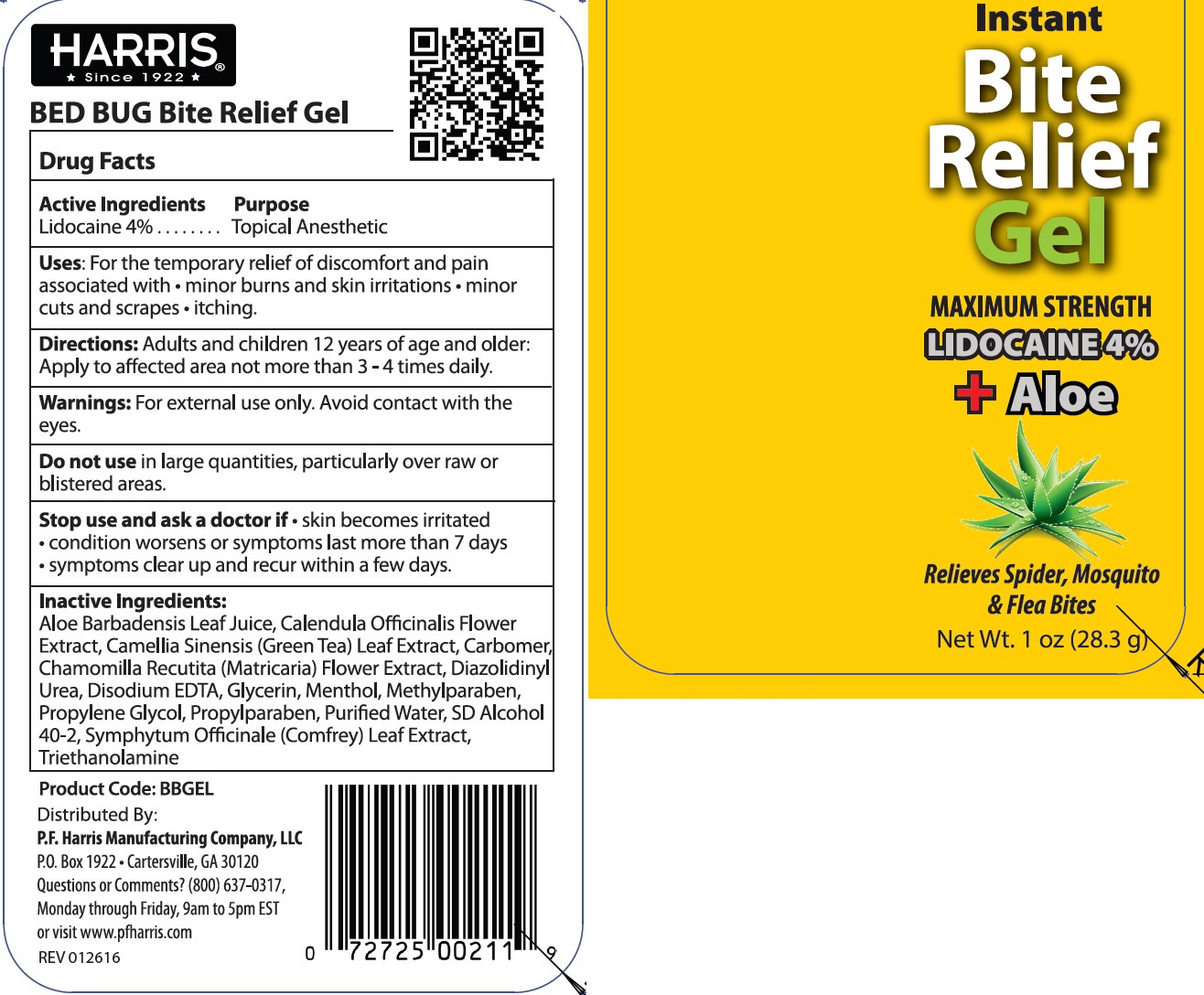 DRUG LABEL: Bed Bug Instant Bite Relief
NDC: 70466-001 | Form: GEL
Manufacturer: P.F. Harris Mfg. Co. LLC
Category: otc | Type: HUMAN OTC DRUG LABEL
Date: 20231109

ACTIVE INGREDIENTS: LIDOCAINE 40 mg/1 g
INACTIVE INGREDIENTS: ALOE VERA LEAF; CALENDULA OFFICINALIS FLOWER; GREEN TEA LEAF; CARBOXYPOLYMETHYLENE; CHAMOMILE; DIAZOLIDINYL UREA; EDETATE DISODIUM; GLYCERIN; MENTHOL; METHYLPARABEN; PROPYLENE GLYCOL; PROPYLPARABEN; WATER; COMFREY LEAF; TROLAMINE

Bed Bug Instant Bite Relief Gel

Active Ingredients

Lidocaine 4%

Purpose

Topical Anesthetic

Uses:

For the temporary relief of discomfort and pain associated with • minor burns and skin irritations • minor cuts and scrapes • itching.

Directions:

Adults and children 12 years of age and older: Apply to affected area not more than 3-4 times daily.

Warnings:

For external use only. Avoid contact with the eyes.

Do not use

in large quantities, particularly over raw or blistered areas.

Stop use and ask a doctor if

•skin becomes irritated • condition worsens or sysmptoms last than 7 days • symptoms clear up and recur within a few days.

Inactive Ingredients:

Aloe Barbadensis Leaf Juice, Calendula Officinalis Flower Extract, Camellia Sinensis (Green Tea) Leaf Extract, Carbomer, Chamomilla Recutita (Matricaria) Flower Extract, Diazolidinyl Urea, Disodium EDTA, Glycerin, Menthol, Methylparaben, Propylene Glycol, Propylparaben, Purified Water, SD Alcohol 40-2, Symphytum Officinale (Comfrey) Leaf Extract, Triethanolamine